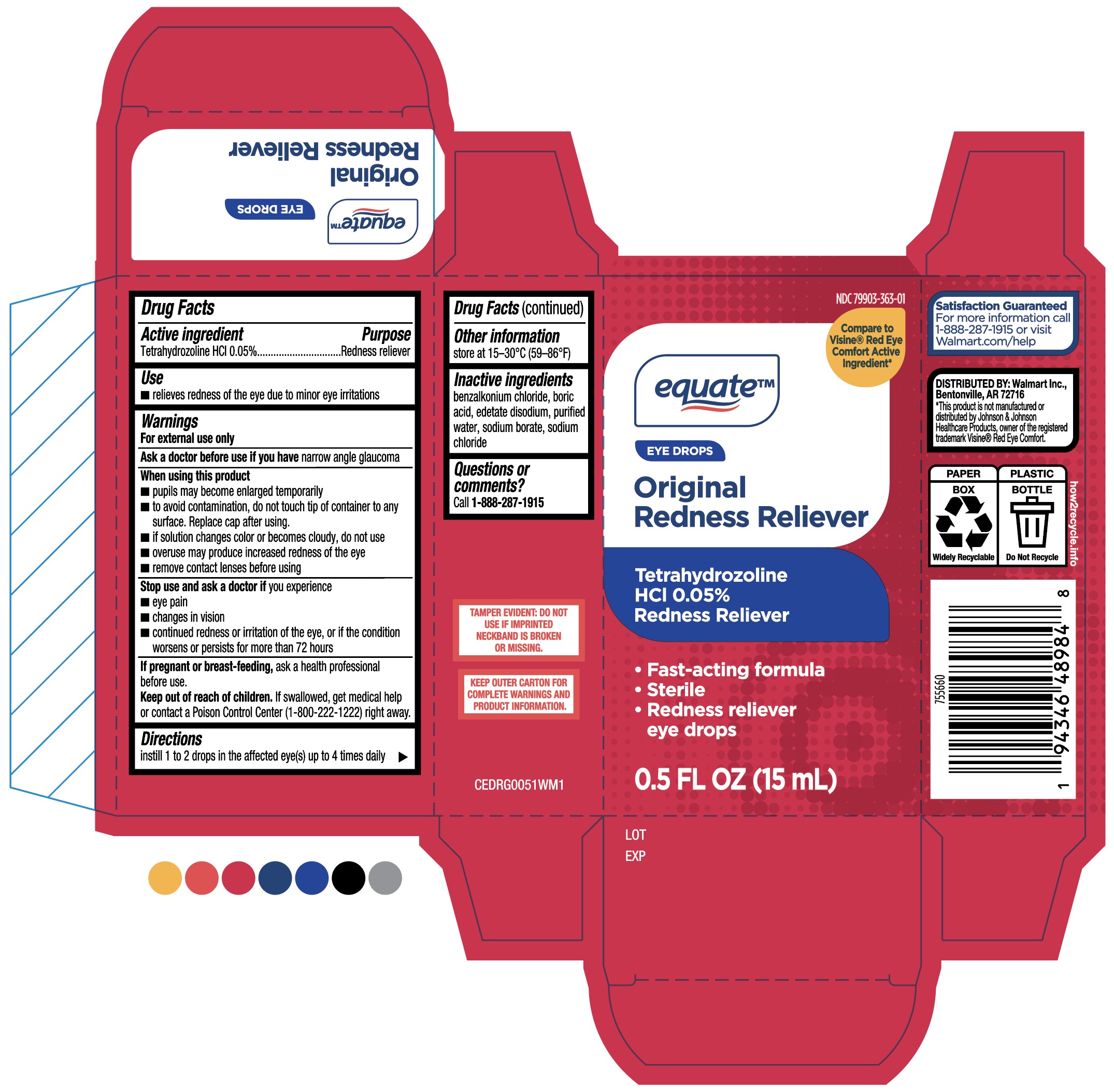 DRUG LABEL: Original Redness Reliever
NDC: 55651-063 | Form: SOLUTION/ DROPS
Manufacturer: KC Pharmaceuticals
Category: otc | Type: HUMAN OTC DRUG LABEL
Date: 20251221

ACTIVE INGREDIENTS: TETRAHYDROZOLINE HYDROCHLORIDE 0.05 g/100 mL
INACTIVE INGREDIENTS: SODIUM CHLORIDE; BENZALKONIUM CHLORIDE; SODIUM BORATE; WATER; EDETATE DISODIUM; BORIC ACID

Equate Original Redness Reliever
KC (MFG) listing for Walmart (PLD) NDC 79903-363-01

Purpose

Redness Reliever

Active ingredient
TetrahydrozolineHCI0.05%

Keep out of reach of children. If swallowed, get medical help or contact a Poison Control Center
(1-800-222-1222) right away.

Inactive ingredients
benzalkonium chloride, boric acid, edetate disodium, purified water, sodium borate, sodium chloride

Directions
instill 1 to 2 drops in the affected eye(s) up to 4times daily

INDICATIONS AND USAGE

■ relieves redness of the eye due to minor eye irritations

Warnings
For external use only
Ask a doctor before use if you have narrow angle glaucoma
When using this product
■ pupils may become enlarged temporarily
■ to avoid contamination, do not touch tip of container to any surface. Replace cap after using.
■ if solution changes color or becomes cloudy, do not use
■ overuse may produce increased redness of the eye
■ remove contact lenses before using
Stop use and ask a doctor if you experience
■ eye pain
■ changes in vision
■ continued redness or irritation of the eye, or if the condition worsens or persists for more
than 72 hours
Hpregnant orbreast-feeding,askahealth professional before use.